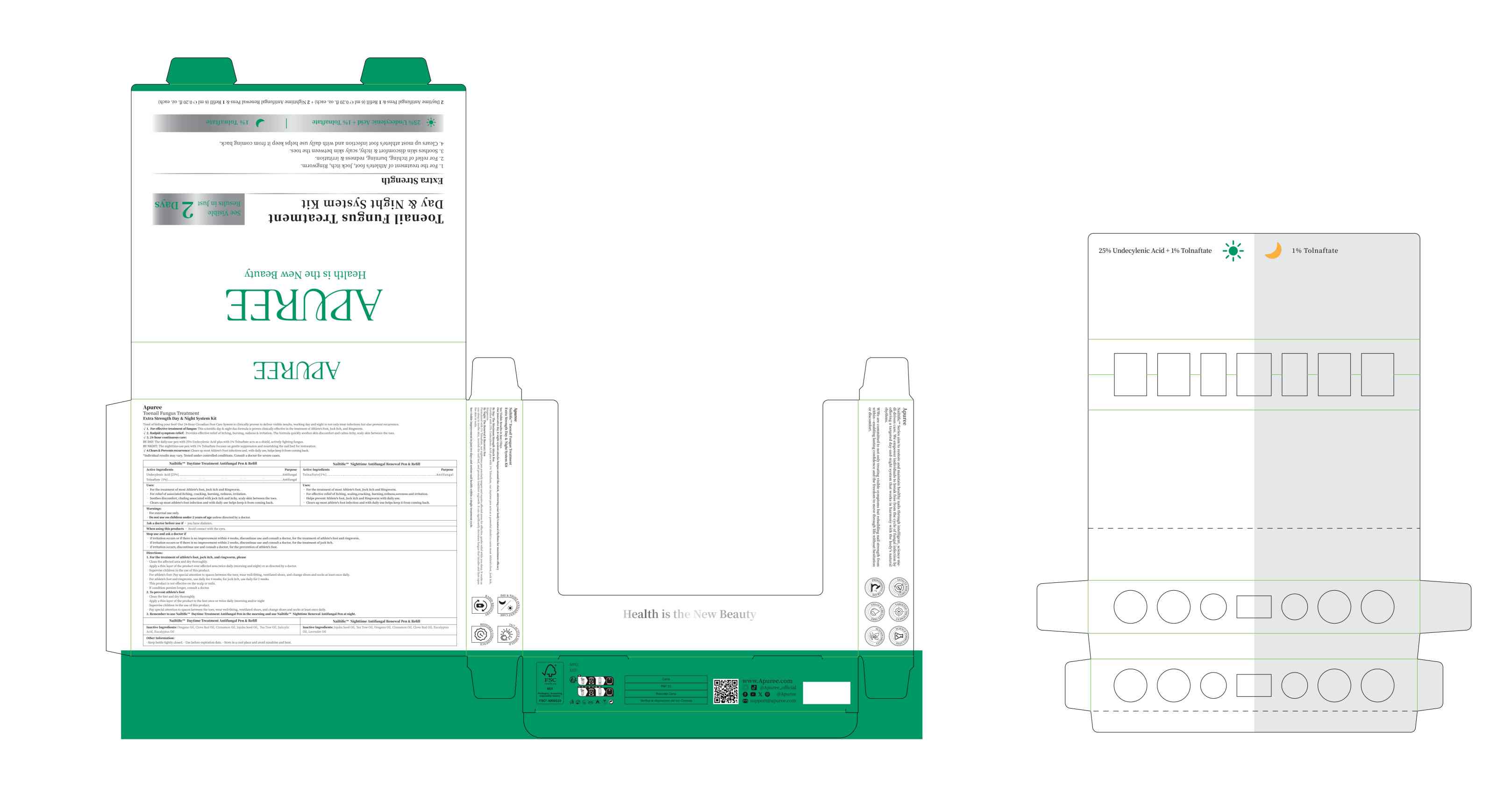 DRUG LABEL: Nailtific Nighttime Antifungal Renewal Pen Refill
NDC: 84167-023 | Form: LIQUID
Manufacturer: Guangzhou Meixi Biotechnology Co., Ltd.
Category: otc | Type: HUMAN OTC DRUG LABEL
Date: 20260129

ACTIVE INGREDIENTS: TOLNAFTATE 0.06 g/6 mL
INACTIVE INGREDIENTS: OREGANO LEAF OIL; CINNAMON OIL; TEA TREE OIL; EUCALYPTUS OIL; JOJOBA OIL; LAVENDER OIL; CLOVE OIL

ACTIVE INGREDIENT

TOLNAFTATE

INACTIVE INGREDIENT

JOJOBA SEED OIL,TEA TREE OIL,OREGANO OIL,CINNAMON OIL,CLOVE BUD OIL,EUCALYPTUS OIL,
LAVENDER OIL

DOSAGE AND ADMINISTRATION

6ml 0.23fl

keep out of reach of children section

warnings section

INDICATIONS AND USAGE

Apply to the affected area twice daily.

PURPOSE

Treatment for nail and skin fungal infections